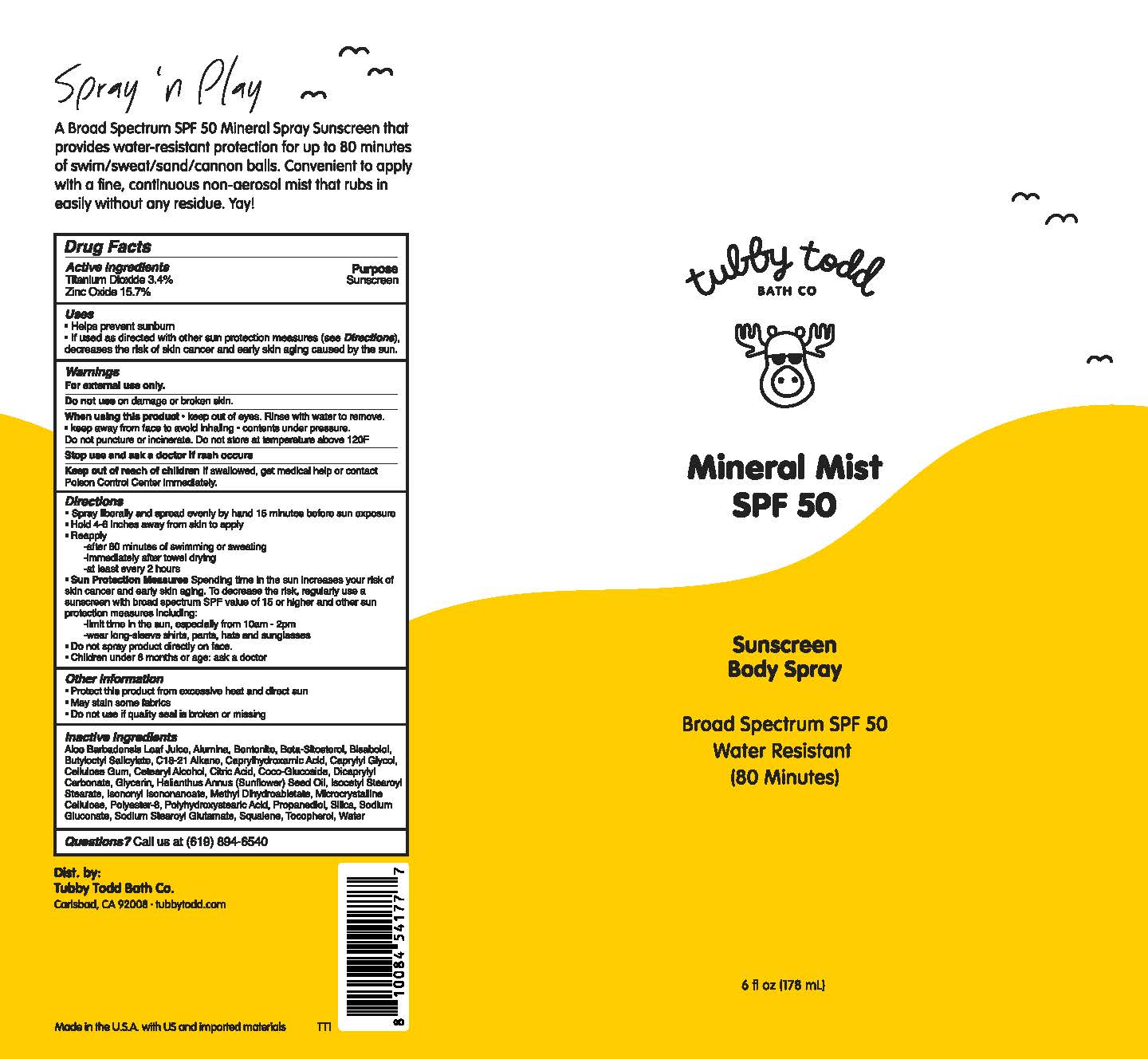 DRUG LABEL: Mineral Mist
NDC: 73088-107 | Form: SPRAY
Manufacturer: TUBBY TODD
Category: otc | Type: HUMAN OTC DRUG LABEL
Date: 20251207

ACTIVE INGREDIENTS: TITANIUM DIOXIDE 3.4 g/100 mL; ZINC OXIDE 15.7 g/100 mL
INACTIVE INGREDIENTS: BETA-SITOSTEROL; ISOCETYL STEAROYL STEARATE; MICROCRYSTALLINE CELLULOSE; POLYESTER-8 (1400 MW, CYANODIPHENYLPROPENOYL CAPPED); SILICON DIOXIDE; SODIUM GLUCONATE; SODIUM STEAROYL GLUTAMATE; TOCOPHEROL; WATER; COCO GLUCOSIDE; ANHYDROUS CITRIC ACID; ALOE VERA LEAF; GLYCERIN; PROPANEDIOL; DICAPRYLYL CARBONATE; ALUMINUM OXIDE; POLYHYDROXYSTEARIC ACID (2300 MW); BENTONITE; .ALPHA.-BISABOLOL, (+)-; BUTYLOCTYL SALICYLATE; C18-C21 ALKANE; CAPRYLHYDROXAMIC ACID; CAPRYLYL GLYCOL; CARBOXYMETHYLCELLULOSE SODIUM, UNSPECIFIED FORM; CETOSTEARYL ALCOHOL; ISONONYL ISONONANOATE; METHYL DIHYDROABIETATE; SQUALENE; HELIANTHUS ANNUUS (SUNFLOWER) SEED OIL

Tubby Todd (as PLD) - Mineral Mist SPF 50 (73088-107)

ACTIVE INGREDIENTS

Titanium Dioxide 3.4%
Zinc Oxide 15.7%

PURPOSE

SUNSCREEN

USES

• Helps prevent sunburn.
• If used as directed with other sun protection measures (see Directions), decreases the risk of skin cancer and early skin aging caused by the sun.

WARNINGS

• For external use only.

• Keep out of reach of children. If swallowed, get medical help or contact Poison Control Center immediately.

• Do not use on damage or broken skin.

• When using this product • keep out of eyes. Rinse with water to remove. • keep away from face to avoid inhaling • contents under pressure. Do not puncture or incinerate. Do not store at temperature above 120 ̊F.

• Stop use and ask a doctor if skin rash occurs.

DIRECTIONS

• Spray liberally and spread evenly by hand 15 minutes before sun exposure.
• Hold 4-6 inches away from skin to apply
• Reapply
-after 80 minutes of swimming or sweating
-immediately after towel drying
-at least every 2 hours
• Sun Protection Measures Spending time in the sun increases your risk of skin cancer and early skin aging. To decrease the risk, regularly use a sunscreen with a broad spectrum SPF value of 15 or higher and other sun protection measures including:
-limit time in the sun, especially from 10am - 2pm
-wear long-sleeve shirts, pants, hats and sunglasses
• Do not spray product directly on face.
• Children under 6 months of age: ask a doctor.

OTHER INFORMATION

• Protect this product from excessive heat and direct sun
• May stain some fabrics
• Do not use if quality seal is broken or missing

INACTIVE INGREDIENT

Aloe Barbadensis Leaf Juice, Alumina, Bentonite, Beta-Sitosterol, Bisabolol, Butyloctyl Salicylate, C18-21 Alkane, Caprylhydroxamic Acid, Caprylyl Glycol, Cellulose Gum, Cetearyl Alcohol, Citric Acid, Coco-Glucoside, Dicaprylyl Carbonate, Glycerin, Helianthus Annuus (Sunflower) Seed Oil, Isocetyl Stearoyl Stearate, Isononyl Isononanoate, Methyl Dihydroabietate, Microcrystalline Cellulose, Polyester-8, Polyhydroxystearic Acid, Propanediol, Silica, Sodium Gluconate, Sodium Stearoyl Glutamate, Squalene, Tocopherol, Water

QUESTIONS?

Call us at (619) 894-6540

Warnings

Directions

Other Information

Inactive ingredients